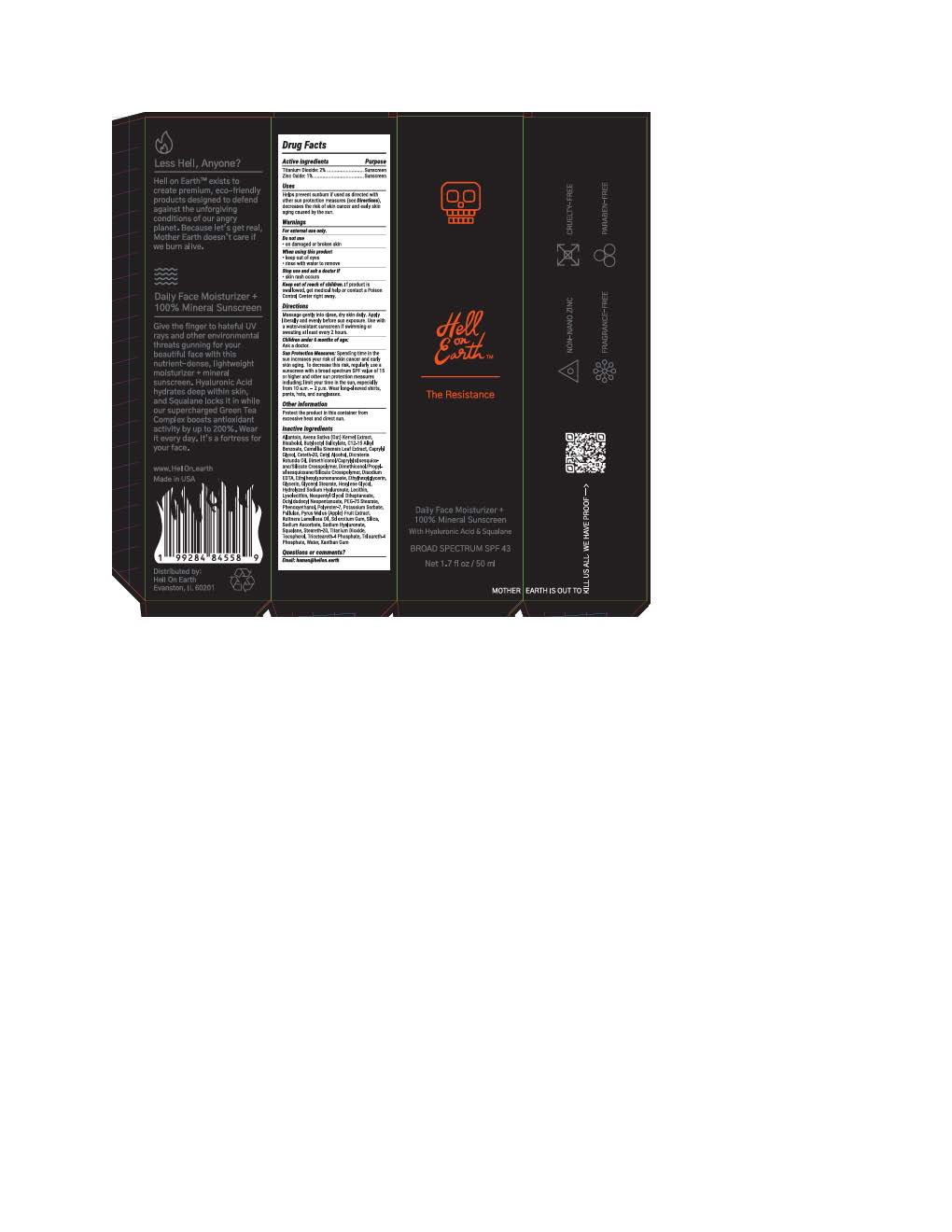 DRUG LABEL: Hell on Earth The Resistance Daily Face Moisturizer
NDC: 85275-391 | Form: LOTION
Manufacturer: Hell on Earth
Category: otc | Type: HUMAN OTC DRUG LABEL
Date: 20251117

ACTIVE INGREDIENTS: ZINC OXIDE 9.7 mg/1 mL; TITANIUM DIOXIDE 19.4 mg/1 mL
INACTIVE INGREDIENTS: POLYESTER-7; GLYCERIN; NEOPENTYL GLYCOL DIHEPTANOATE; GLYCERYL STEARATE SE; ALKYL (C12-15) BENZOATE; ALLANTOIN; CAPRYLYL GLYCOL; AVENA SATIVA WHOLE; DICRATERIA ROTUNDA OIL; DISODIUM EDTA-COPPER; CAMELLIA SINENSIS WHOLE; BUTYLOCTYL SALICYLATE; TRICETEARETH-4 PHOSPHATE; PULLULAN; XANTHAN GUM; STEARETH-20; HEXYLENE GLYCOL; TRILAURETH-4 PHOSPHATE; SODIUM ASCORBATE; OCTYLDODECYL NEOPENTANOATE; CETYL ALCOHOL; SQUALANE; PEG-75 STEARATE; PHENOXYETHANOL; .ALPHA.-BISABOLOL, (+)-; ETHYLHEXYLGLYCERIN; DIMETHICONOL/PROPYLSILSESQUIOXANE/SILICATE CROSSPOLYMER (450000000 MW); LECITHIN, SOYBEAN; SILICON DIOXIDE; ETHYLHEXYL ISONONANOATE; CETETH-20; POTASSIUM SORBATE; TOCOPHEROL; RUTTNERA LAMELLOSA OIL

Hell on Earth The Resistance Daily Face Moisturizer